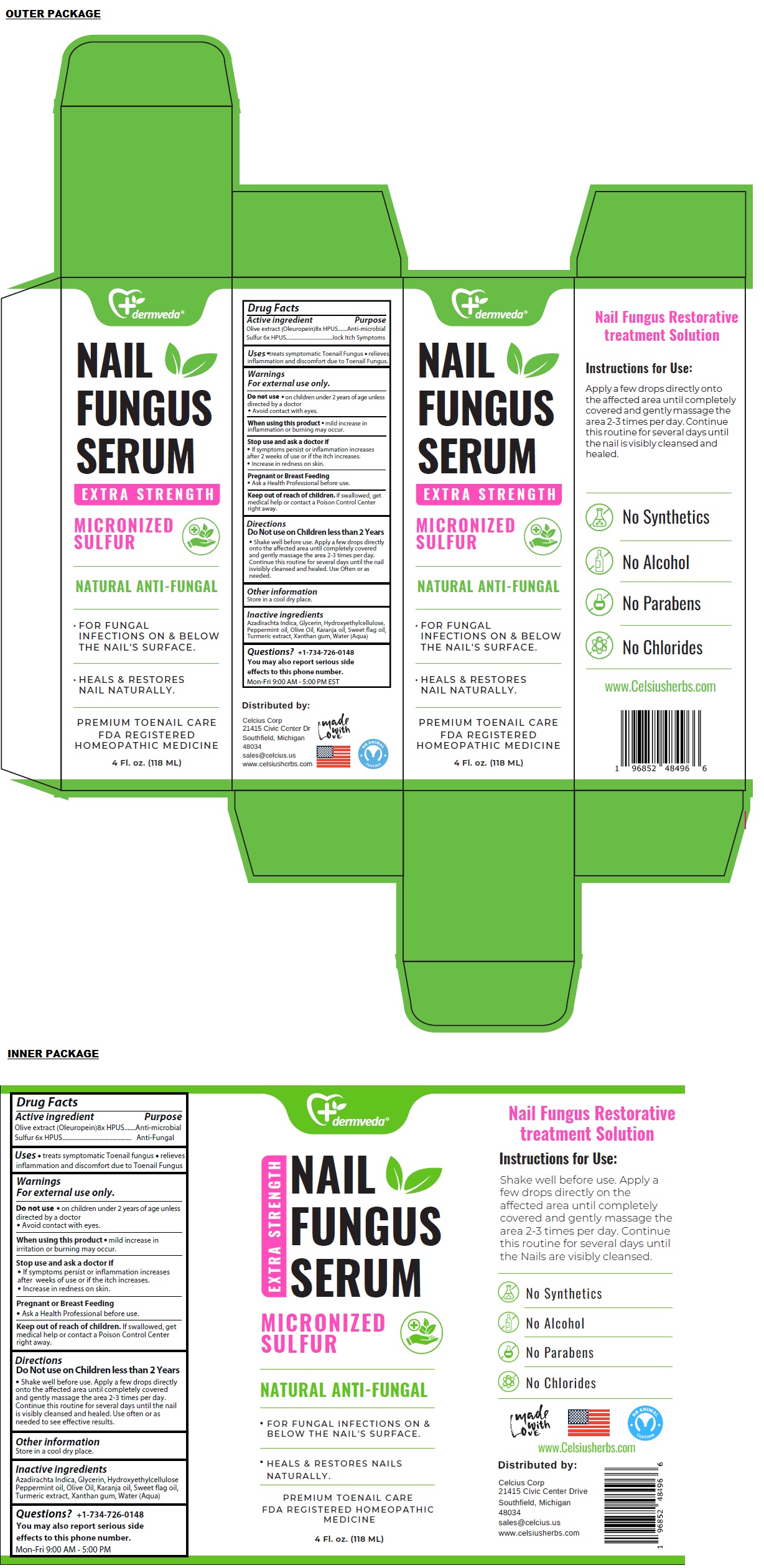 DRUG LABEL: dermveda NAIL FUNGUS SERUM
NDC: 83819-120 | Form: SOLUTION
Manufacturer: Celcius Corp.
Category: homeopathic | Type: HUMAN OTC DRUG LABEL
Date: 20260209

ACTIVE INGREDIENTS: OLEA EUROPAEA (OLIVE) LEAF POWDER 8 [hp_X]/118 mL; SULFUR 6 [hp_X]/118 mL
INACTIVE INGREDIENTS: AZADIRACHTA INDICA SEED OIL; GLYCERIN; HYDROXYETHYL CELLULOSE, UNSPECIFIED; PEPPERMINT OIL; OLIVE OIL; KARUM SEED OIL; CALAMUS OIL; TURMERIC; XANTHAN GUM; WATER

dermveda™ NAIL FUNGUS SERUM

Active ingredient

Olive extract (Oleuropein) 8x HPUS
Sulfur 6x HPUS

Purpose

Anti-microbial
Jock Itch Symptoms

Uses

• treats symptomatic Toenail Fungus • relieves inflammation and discomfort due to Toenail Fungus.

Warnings

For external use only.

Do not use • on children under 2 years of age unless directed by a doctor.
• Avoid contact with eyes.

When using this product • mild increase in inflammation or burning may occur.

Stop use and ask a doctor if
• If symptoms persist or inflammation increases after 2 weeks of use or if the itch increases.
• Increase in redness on skin.

Pregnant or Breast Feeding
• Ask a Health Professional before use.

Keep out of reach of children. If swallowed, get medical help or contact a Poison Control Center right away.

Directions

Do Not use on Children less than 2 Years

• Shake well before use. Apply a few drops directly onto the affected area until completely covered and gently massage the area 2-3 times per day. Continue this routine for several days until the nail is visibly cleansed and healed. Use Often or as needed to see effective results.

Other information

Store in a cool dry place.

Inactive ingredients

Azadirachta Indica, Glycerin, Hydroxyethylcellulose, Peppermint oil, Olive Oil, Karanja oil, Sweet flag oil, Turmeric extract, Xanthan gum, Water (Aqua)

Questions?

+1-734-726-0148
You may also report serious side effects to this phone number.
Mon-Fri 9:00 AM - 5:00 PM EST

EXTRA STRENGTH

MICRONIZED SULFUR

NATURAL ANTI-FUNGAL

• FOR FUNGAL INFECTIONS ON & BELOW THE NAIL'S SURFACE.
• HEALS & RESTORES NAIL NATURALLY.

PREMIUM TOENAIL CARE
FDA REGISTERED
HOMEOPATHIC MEDICINE

Nail Fungus Restorative treatment Solution

No Synthetics
No Alcohol
No Parabens
No Chlorides

Distributed by:

Celcius Corp
21415 Civic Center Dr
Southfield, Michigan
48034
sales@celcius.us
www.celsiusherbs.com

made with Love

NO ANIMAL TESTING